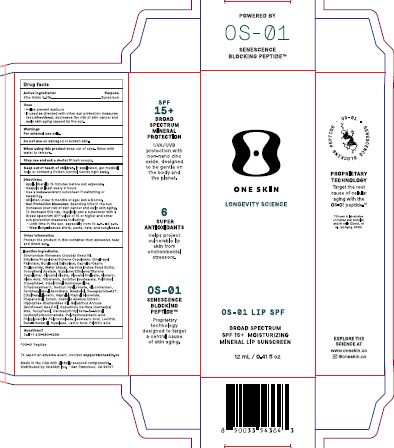 DRUG LABEL: OS-01 Lip SPF BS SPF15
NDC: 84451-004 | Form: CREAM
Manufacturer: ONESKIN INC.
Category: otc | Type: HUMAN OTC DRUG LABEL
Date: 20250514

ACTIVE INGREDIENTS: ZINC OXIDE 5.5 g/100 g
INACTIVE INGREDIENTS: OLEIC ACID; BISABOLOL; ETHYLHEXYLGLYCERIN; PROPYLENE; HELIANTHUS ANNUUS (SUNFLOWER) SEED OIL; SODIUM HYALURONATE; GLYCERYL DIOLEATE; ECTOIN; ETHYLHEXYL PALMITATE; TRIBEHENIN; SIMMONDSIA CHINENSIS (JOJOBA) SEED OIL; .ALPHA.-TOCOPHEROL ACETATE; DIPALMITOYL HYDROXYPROLINE; POLYHYDROXYSTEARIC ACID (2300 MW); GLYCERIN; TRIHYDROXYSTEARIN; WATER; GARCINIA INDICA SEED BUTTER; GLYCERYL OLEATE; SQUALENE; LACTIC ACID; GLUCOMANNAN; POLYGLYCERYL-3 PENTARICINOLEATE; ETHYLENE; BUTYLOCTYL SALICYLATE; HIPPOPHAE RHAMNOIDES SEED OIL; ISOSTEARIC ACID; LECITHIN, SUNFLOWER; TETRAHEXYLDECYL ASCORBATE; SORBITAN ISOSTEARATE; CAPRYLIC/CAPRIC TRIGLYCERIDE; 1-BUTENE; PALMITOYL TRIPEPTIDE-1; CAPRYLYL/CAPRYL GLUCOSIDE; PROPANEDIOL; CENTELLA ASIATICA TRITERPENOIDS; CARNAUBA WAX; TOCOPHEROL; PENTAERYTHRITYL TETRA-DI-T-BUTYL HYDROXYHYDROCINNAMATE; BETA-SITOSTEROL; PALMITIC ACID

Drug Facts

Active ingredie:
Zinc Oxide 5.5%.

Purpose: Sunscreen

Uses
• Helps prevent sunburn
• If used as directed with other sun protection measures (see Directions), decreases the risk of skin cancer and early skin aging caused by the sun.

Warnings
For external use only

Do not use on damaged or broken skin.

When using this product keep out of eyes. Rinse with water to remove.

Stop use and ask a doctor if rash occurs.

Keep out of reach of children. If swallowed, get medical help or contact a Poison Control Center right away.

Directions:
• Apply liberally 15 minutes before sun exposure.
• Reapply at least every 2 hours
• Use a water-resistant sunscreen If swimming or sweating.
• Children under 8 months of age: Ask a Doctor.
• Sun Probation Measures: Spending time in the sun increases your risk of skin cancer and early skin aging.
To decrease this risk, regularly use a sunscreen with a Broad Spectrum SPF value of 15 or higher and other sun protection measures including:
• Limit time in the sun. especially from 10 a.m. - 2 p.m.
• Wear long-sleeved shirts, pants, hats, and sunglasses

Other information
Protect the product in this container from excessive heat and direct sun.

Inactive Ingredients
Simmondsia Chinensis (Jojoba) Seed Oil, Ethylene/Propylene/Styrene Copolymer, Ethylhexyl
Palmitate, Butyl octyl Salicylate. Caprylic/Capric Triglyceride, Water (Aqua), Garcinia Indica Seed Butter, Tocopheryl Acetate, Butylene/Ethylene/Styrene Copolymer, Glyceryl Oleate, Glyceryl Dioleate, Glycerin, Oleic Acid, Tribehenin, Sorbitan Isostearate, Palmitoyl Tripeptide-1, Dipalmitoyl Hydroxyproline, Trihydroxystearin, Sodium Hyaluronate, Glucomannan, Tetrahexyldecyl Ascorbate, Bisabolol, Decapeptide-52*,Ethylhexylglycerin, Caprylyl/Capryl Glucoside, Propanediol, Ectoin, Centella Asiatica Extract, Hippophae Rhamnoides oil, Helianthus Annuus (Sunflower) Seed Oil, Copernicia Cerifera (Carnauba)Wax, Tocopherol, Pentaerythrityl Tetra-di-t-butyl Hydroxyhydrocinnamate, Polyhydroxy stearic Acid, Polyglyceryl-3 Polyricinoleate, Isostearic Acid, Lecithin, Beta-Sitosterol, Squalene, Lactic Acid, Palmitic acid.